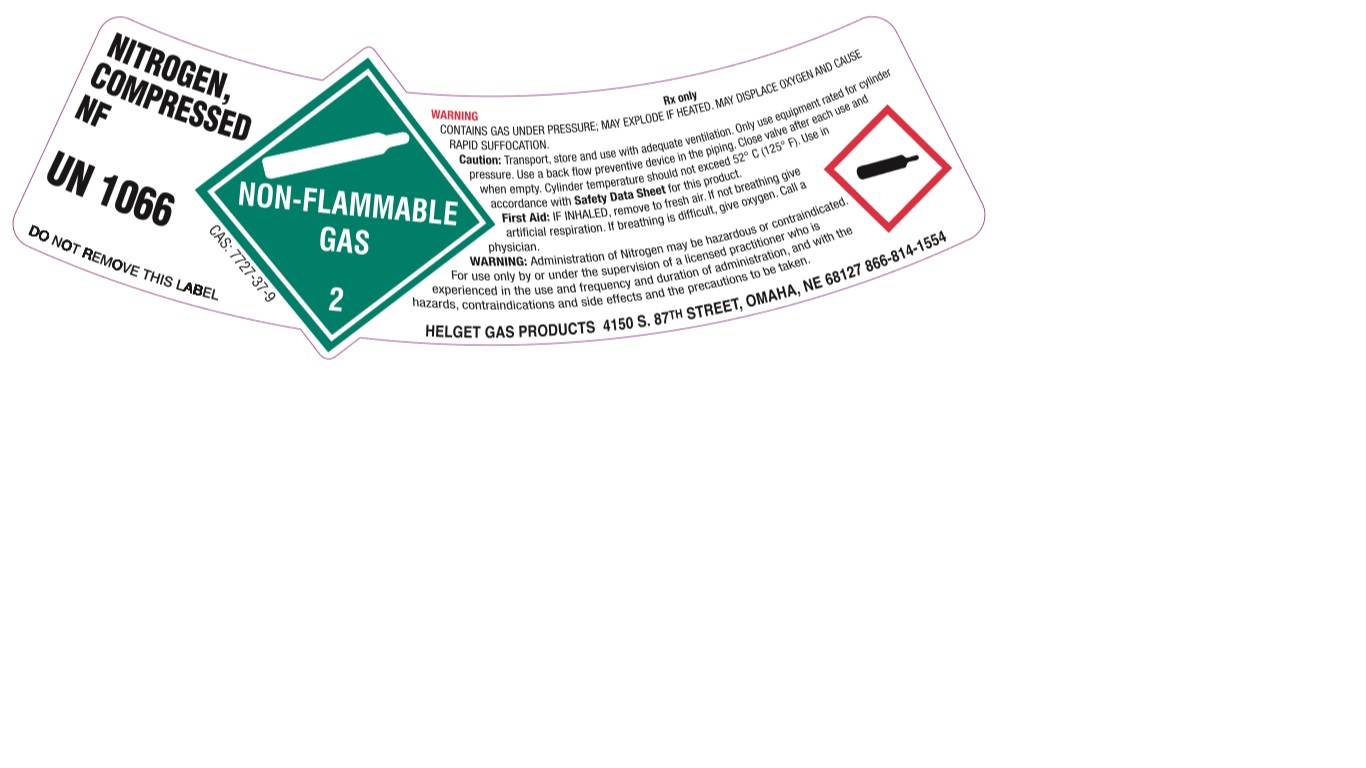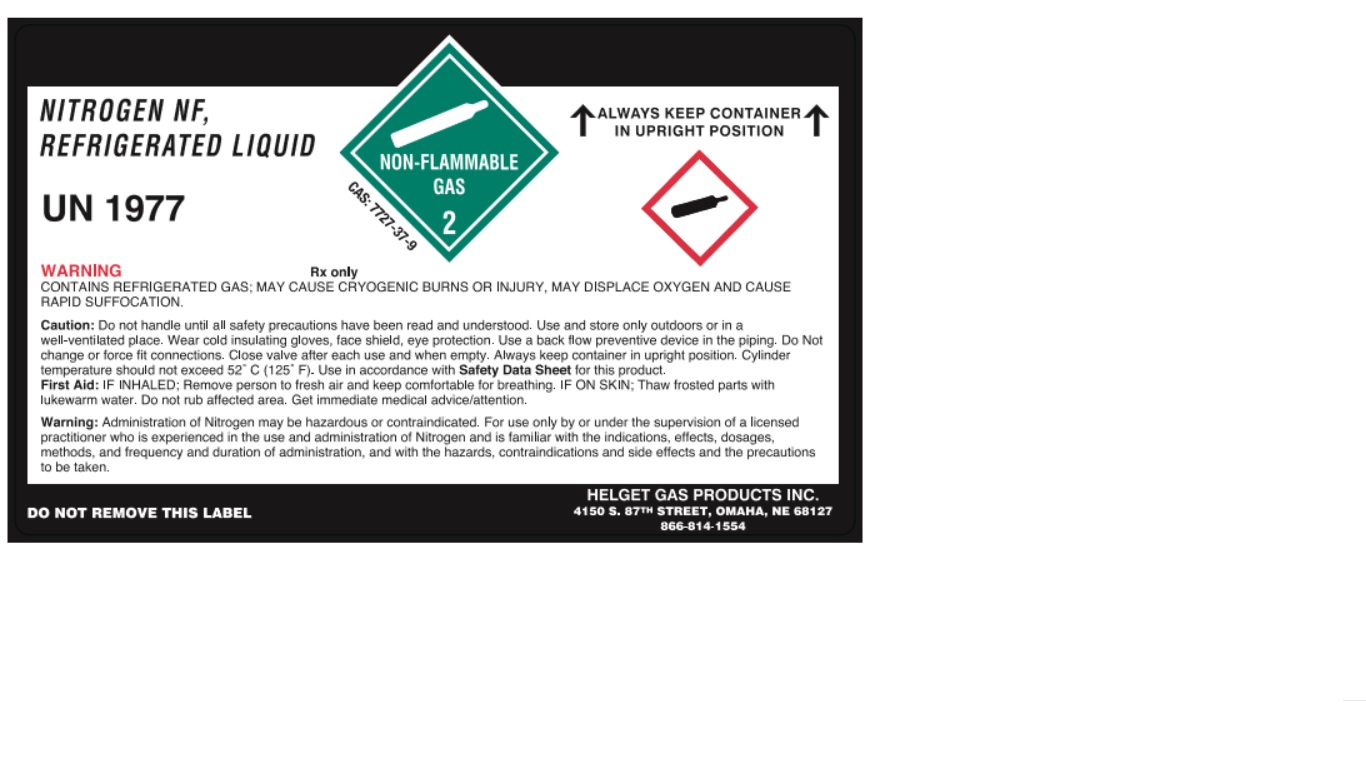 DRUG LABEL: Nitrogen
NDC: 52086-012 | Form: GAS
Manufacturer: Helget Gas Products
Category: prescription | Type: HUMAN PRESCRIPTION DRUG LABEL
Date: 20251112

ACTIVE INGREDIENTS: NITROGEN 990 mL/1 L

Nitrogen -012

PACKAGE LABEL

NITROGEN NF, REFRIGERATED LIQUID
UN1977
ALWAYS KEEP CONTAINER IN UPRIGHT POSITION
CAS: 7727-37-G
WARNING
Rx only
CONTAINS REFRIGERATED GAS; MAY CAUSE CRYOGENIC BURNS OR INJURY, MAY DISPLACE OXYGEN AND CAUSE RAPID SUFFOCATION.
Caution: Do not handle until all safety precautions have been read and understood. Use and store only outdoors or in a well-ventilated place. Wear cold insulating gloves, face shield, eye protection. Use a back flow preventive device in the piping. Do Not change or force fit connections. Close valve after each use and when empty. Always keep container in upright position. Cylinder temperature should not exceed 52 C (125F). Use in accordance with Safety Data Sheet for this product.
First Aid: IF INHALED; remove person to fresh air and keep comfortable for breathing. IF ON SKIN; Thaw frosted parts with lukewarm water. Do not rub affected area. Get immediate medical advice/attention.
Warning: Administration of Nitrogen may be hazardous or contraindicated. For use only by or under the supervision of a licensed practitioner who is experienced in the use and administration of Nitrogen and is familiar with the indications, effects, dosages, methods, and frequency and duration of administration, and with the hazards, contraindications and side effects and the precautions to be taken.
DO NOT REMOVE THIS LABEL
HELGET GAS PRODUCTS INC.
4150 S. 87TH STREET, OMAHA, NE 68127
866-814-1554

PACKAGE LABEL

NITROGEN, COMPRESSED NF
UN1066
CAS: 7727-37-G
DO NOT REMOVE THIS LABEL
WARNING
Rx only
CONTAINS GAS UNDER PRESSURE; MAY EXPLODE IF HEATED. MAY DISPLACE OXYGEN AND CAUSE RAPID SUFFOCATION.
Caution: Transport, store and use with adequate ventilation. Only use equipment rated for cylinder pressure. Use a back flow preventive device in the piping. Close valve after each use and when empty. Cylinder temperature should not exceed 52 C (125 F). Use in accordance with Safety Data Sheet for this product.
First Aid: IF INHALED, remove to fresh air. If not breathing give artificial respiration. If breathing is difficult, give oxygen. Call a physician.
WARNING: Administration of Nitrogen may be hazardous or contraindicated. For use only by or under the supervision of a licensed practitioner who is experienced in the use and frequency and duration of administration, and with the hazards, contraindications and side effects and the precautions to be taken.
HELGET GAS PRODUCTS 4150 S 87TH STREET, OMAHA, NE 68127 866-814-1554